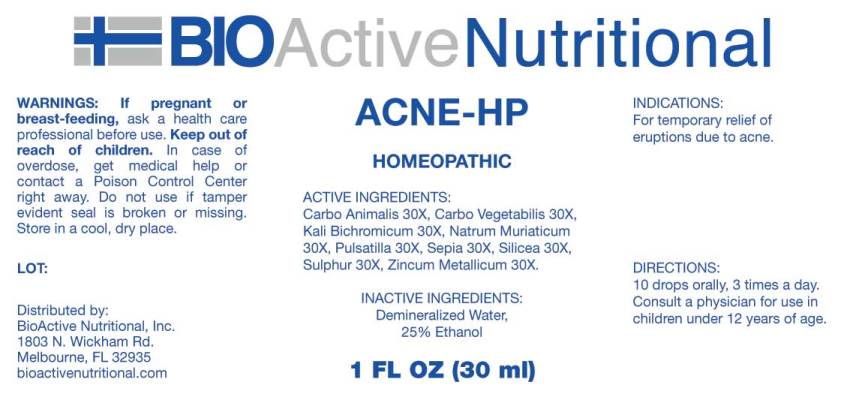 DRUG LABEL: Acne
NDC: 43857-0275 | Form: LIQUID
Manufacturer: BioActive Nutritional, Inc.
Category: homeopathic | Type: HUMAN OTC DRUG LABEL
Date: 20170620

ACTIVE INGREDIENTS: CARBO ANIMALIS 30 [hp_X]/1 mL; ACTIVATED CHARCOAL 30 [hp_X]/1 mL; POTASSIUM DICHROMATE 30 [hp_X]/1 mL; SODIUM CHLORIDE 30 [hp_X]/1 mL; PULSATILLA VULGARIS 30 [hp_X]/1 mL; SEPIA OFFICINALIS JUICE 30 [hp_X]/1 mL; SILICON DIOXIDE 30 [hp_X]/1 mL; SULFUR 30 [hp_X]/1 mL; ZINC 30 [hp_X]/1 mL
INACTIVE INGREDIENTS: WATER; ALCOHOL

Drug Facts:

ACTIVE INGREDIENTS:

Carbo Animalis 30X, Carbo Vegetabilis 30X, Kali Bichromicum 30X, Natrum Muriaticum 30X, Pulsatilla (Vulgaris) 30X, Sepia 30X, Silicea 30X, Sulphur 30X, Zincum Metallicum 30X.

INDICATIONS:

For temporary relief of eruptions due to acne.

WARNINGS:

If pregnant or breast-feeding, ask a health care professional before use.

Keep out of reach of children. In case of overdose, get medical help or contact a Poison Control Center right away.

Do not use if tamper evident seal is broken or missing.

Store in cool, dry place.

Keep out of reach of children. In case of overdose, get medical help or contact a Poison Control Center right away.

DIRECTIONS:

10 drops orally, 3 times a day. Consult a physician for use in children under 12 years of age.

INDICATIONS:

For temporary relief of eruptions due to acne.

INACTIVE INGREDIENTS:

Demineralized Water, 25% Ethanol

QUESTIONS:

Distributed by:

BioActive Nutritional, Inc.

1803 N. Wickham Rd.

Melbourne, FL 32935

bioactivenutritional.com

PACKAGE LABEL DISPLAY:

BIOActive Nutritional

ACNE-HP

HOMEOPATHIC

1 FL OZ (30 ml)